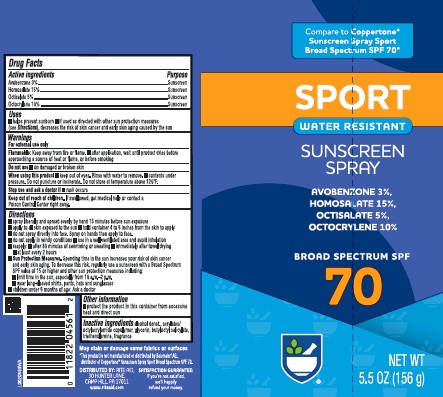 DRUG LABEL: Sunscreen
NDC: 11822-1013 | Form: SPRAY
Manufacturer: Rite Aid Corporation
Category: otc | Type: HUMAN OTC DRUG LABEL
Date: 20260202

ACTIVE INGREDIENTS: AVOBENZONE 90 mg/1 g; HOMOSALATE 225 mg/1 g; OCTISALATE 250 mg/1 g; OCTOCRYLENE 1000 mg/1 g
INACTIVE INGREDIENTS: ALCOHOL; CYCLOMETHICONE 5; GLYCERIN; BUTYLOCTYL SALICYLATE; TROLAMINE

Rite Aid_Daylogic 958.000/958AA
Sport Sunscreen Spray SPF 70

Active Ingredients

Avobenzone 3%

Homosalate 15%

Octisalate 5%

Octocrylene 10%

Purpose

Sunscreen

Uses

- helps prevent sunburn
- if used as directed with other skin protection measures (see Directions), decreases the risk of skin cancer and early skin aging caused by the sun.

Warnings

For external use only

Flammable

Keep away from fire or flame.

- after application, wait until product dries before approaching a souce of heat or flame, or before smoking

Do not use

- On damaged or broken skin

When using this product

- Keep out of eyes. Rinse with water to remove. Contents under pressure. Do not puncture or incinerate. Do not store at temperature above 120°F.

Stop use and ask a doctor

if rash occurs

Keep out of reach of children

If swallowed, get medical help or contact a Poison Control Center right away.

directions

■ spray liberally and spread evenly by hand 15 minutes before sun exposure
■ apply to all skin exposed to the sun
■ hold container 4 to 6 inches from the skin to apply
■ do not spray directly into face. Spray on hands then apply to face.
■ do not apply in windy conditions
■ use in a well-ventilated area and avoid inhalation
■ reapply:

- after 80 minutes of swimming or sweating
- immediately after towel drying
- at least every 2 hours

■ Sun Protection Measures. Spending time in the sun increases your risk of skin cancer and early skin aging. To decrease this risk, regularly use a sunscreen with a Broad Spectrum SPF value of 15 or higher and other sun protection measures including:

- limit time in the sun, especially from 10 a.m.–2 p.m.
- wear long-sleeved shirts, pants, hats and sunglasses

■ children under 6 months of age: Ask a doctor

Other information

- protect the product in the container from excessive heat and direct sun

Inactive ingredients

alcohol denat., acrylates/octylacrylamide copolymer, glycerin, butyloctyl salicylate, triethanolamine, fragrance

Disclaimers

May stain or damage some fabrics or surfaces

*This prosduct is not manufactured or distrubted by Beiersdorf AG, distributer of CoppertoneSunscreen Spray Sport Broad Spectrum SPF 70.

ADVERSE REACTION

DISTRIBUTED BY:

RITE AID, 30 HUNTER LANE

CAMP HILL, PA 1711

www.riteaid.com

SATISFACTION GUARANTEE:

if you're not satisfied,

we'll happily refund your money.

Principal Panel Display

Compare to Coppertone®Sunscreen Spray Sport Broad Spectrum SPF 70*

SPORT

WATER RESISTANT

SUNSCREEN SPRAY

Avobenzone 3%

Homosalate 15%

Octisalate 5%

Octocrylene 10%

Broad Spectrum SPF 70

NET WT 5.5 OZ (156 g)